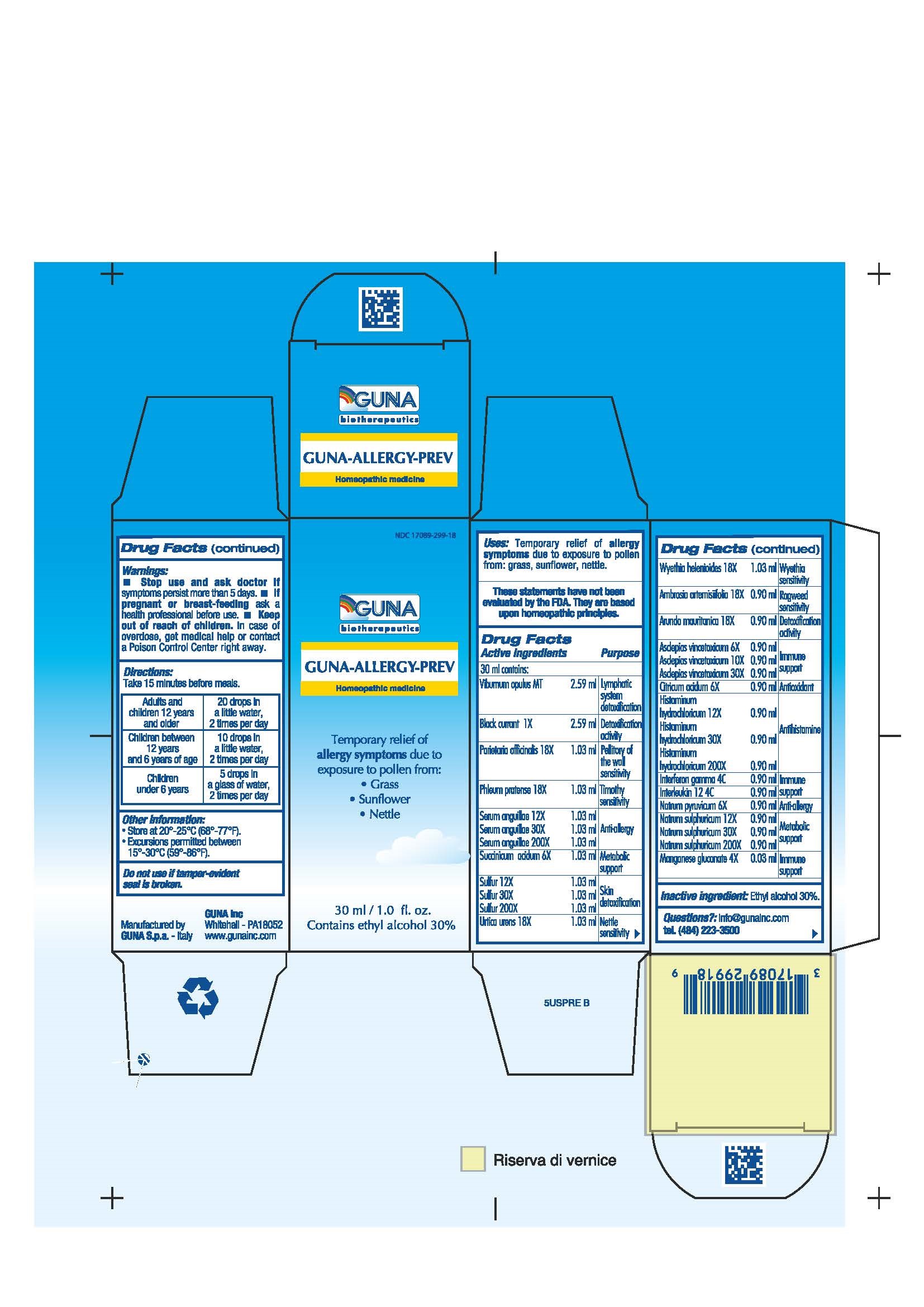 DRUG LABEL: GUNA-ALLERGY-PREV
NDC: 17089-299 | Form: SOLUTION/ DROPS
Manufacturer: Guna spa
Category: homeopathic | Type: HUMAN OTC DRUG LABEL
Date: 20181221

ACTIVE INGREDIENTS: AMBROSIA ARTEMISIIFOLIA 18 [hp_X]/30 mL; ARUNDO PLINIANA ROOT 18 [hp_X]/30 mL; ASCLEPIAS CURASSAVICA 6 [hp_X]/30 mL; BLACK CURRANT 1 [hp_X]/30 mL; CITRIC ACID MONOHYDRATE 6 [hp_X]/30 mL; HISTAMINE DIHYDROCHLORIDE 30 [hp_X]/30 mL; INTERFERON GAMMA-1B 4 [hp_C]/30 mL; HUMAN INTERLEUKIN 12 4 [hp_C]/30 mL; MANGANESE GLUCONATE 4 [hp_X]/30 mL; SODIUM PYRUVATE 6 [hp_X]/30 mL; SODIUM SULFATE 200 [hp_X]/30 mL; PARIETARIA OFFICINALIS 18 [hp_X]/30 mL; PHLEUM PRATENSE 18 [hp_X]/30 mL; ANGUILLA ROSTRATA BLOOD SERUM 200 [hp_X]/30 mL; SUCCINIC ACID 6 [hp_X]/30 mL; SULFUR 30 [hp_X]/30 mL; URTICA URENS 18 [hp_X]/30 mL; VIBURNUM OPULUS ROOT 3 g/30 mL; WYETHIA HELENIOIDES ROOT 18 [hp_X]/30 mL
INACTIVE INGREDIENTS: ALCOHOL

GUNA-ALLERGY PREV

ACTIVE INGREDIENTS/PURPOSE

AMBROSIA ARTEMISIIFOLIA 18X RAGWEED SENSITIVITY
ARUNDO MAURITANICA 18X DETOXIFICATION ACTIVITY
ASCLEPIAS VINCETOXICUM 6X, 10X, 30X IMMUNE SUPPORT
BLACK CURRANT 1X DETOXIFICATION ACTIVITY
CITRICUM ACIDUM 6X ANTIOXIDANT
HISTAMINUM HYDROCHLORICUM 12X, 30X, 200X ANTIHISTAMINE
INTERFERON GAMMA 4C IMMUNE SUPPORT
INTERLEUKIN 12 4C IMMUNE SUPPORT
MANGANESE GLUCONATE 4X IMMUNE SUPPORT
NATRUM PYRUVICUM 6X ANTI-ALLERGY
NATRUM SULF 12X, 30X, 200X METABOLIC SUPPORT
PARIETARIA OFFICINALIS 18X PELLITORY OF THE WALL SENSITIVITY
PHLEUM PRATENSE 18X TIMOTHY SENSITIVITY
SERUM ANGUILLAE 12X, 30X, 200X ANTI-ALLERGY
SUCCINICUM ACIDUM 6X METABOLIC SUPPORT
SULFUR 12X, 30X, 200X SKIN DETOXIFICATION
URTICA URENS 18X NETTLE SENSITIVITY
VIBURNUM OPULUS T LYMPHATIC SYSTEM DETOXIFICATION
WYETHIA HELENIOIDES 18X WYETHIA SENSITIVITY

USES

Temporary relief of allergy symptoms due to exposure to pollen from:

- Grass
- Sunflower
- Nettle

WARNINGS

- Stop use and ask doctor if symptoms persist more than 5 days.
- If pregnant or breast-feeding ask a health professional before use.
- Keep out of reach of children. In case of overdose, get medical help or contact a Poison Control Center right away.
- Contains ethyl alcohol 30%

PREGNANCY

If pregnant or breast-feeding ask a doctor before use

WARNINGS

Keep out of reach of children

DIRECTIONS

For maximum symptom relief start before the anticipated allergen exposure.
Adults and children 12 years and older 20 drops in a little water, 2 times per day
Children between 12 years and 6 years of age 10 drops in a little water, 2 times per day
Children under 6 years 5 drops in a glass of water, 2 times per day

QUESTIONS

Questions?: info@gunainc.com, tel. (484) 223-3500

INDICATIONS AND USAGE

Take 15 minutes before meals

Inactive ingredient: Ethyl alcohol 30%.